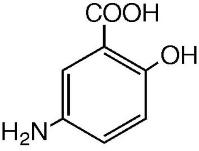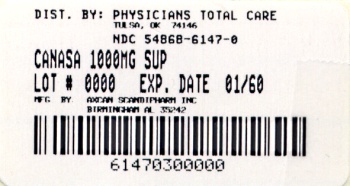 DRUG LABEL: Canasa
NDC: 54868-6147 | Form: SUPPOSITORY
Manufacturer: Physicians Total Care, Inc.
Category: prescription | Type: HUMAN PRESCRIPTION DRUG LABEL
Date: 20100823

ACTIVE INGREDIENTS: MESALAMINE 1000 mg/1 1
INACTIVE INGREDIENTS: FAT, HARD

DESCRIPTION

The active ingredient in CANASA® 1000 mg suppositories is mesalamine, also known as mesalazine or 5-aminosalicylic acid (5-ASA). Chemically, mesalamine is 5-amino-2-hydroxybenzoic acid, and is classified as an anti-inflammatory drug.

The empirical formula is C7H7NO3, representing a molecular weight of 153.14. The structural formula is:

Each CANASA® rectal suppository contains 1000 mg of mesalamine (USP) in a base of Hard Fat, NF.

CLINICAL PHARMACOLOGY

Sulfasalazine has been used in the treatment of ulcerative colitis for over 55 years. It is split by bacterial action in the colon into sulfapyridine (SP) and mesalamine (5-ASA). It is thought that the mesalamine component only is therapeutically active in ulcerative colitis.

Mechanism of Action

The mechanism of action of mesalamine (and sulfasalazine) is not fully understood, but appears to be topical rather than systemic. Although the pathology of inflammatory bowel disease is uncertain, both prostaglandins and leukotrienes have been implicated as mediators of mucosal injury and inflammation. Recently, however, the role of mesalamine as a free radical scavenger or inhibitor of tumor necrosis factor (TNF) has also been postulated.

Pharmacokinetics Absorption:

Mesalamine (5-ASA) administered as a rectal suppository is variably absorbed. In patients with ulcerative colitis treated with mesalamine 500 mg rectal suppositories, administered once every eight hours for six days, the mean mesalamine peak plasma concentration (Cmax) was 353 ng/mL (CV=55%) following the initial dose and 361 ng/mL (CV=67%) at steady state. The mean minimum steady state plasma concentration (Cmin) was 89 ng/mL (CV=89%). Absorbed mesalamine does not accumulate in the plasma.

Distribution:

Mesalamine administered as rectal suppositories distributes in rectal tissue to some extent. In patients with ulcerative proctitis treated with CANASA® (mesalamine, USP) 1000 mg rectal suppositories, rectal tissue concentrations for 5-ASA and N-acetyl-5-ASA have not been rigorously quantified.

Metabolism:

Mesalamine is extensively metabolized, mainly to N-acetyl-5-ASA. The site of metabolism has not been elucidated. In patients with ulcerative colitis treated with one 500 mg mesalamine rectal suppository every eight hours for six days, peak concentration (Cmax) of N-acetyl-5-ASA ranged from 467 ng/mL to 1399 ng/mL following the initial dose and from 193 ng/mL to 1304 ng/mL at steady state.

Elimination:

Mesalamine is eliminated from plasma mainly by urinary excretion, predominantly as N-acetyl-5-ASA. In patients with ulcerative proctitis treated with one mesalamine 500 mg rectal suppository every eight hours for six days, ≤ 12% of the dose was eliminated in urine as unchanged 5-ASA and 8-77% as N-acetyl-5-ASA following the initial dose. At steady state, ≤ 11% of the dose was eliminated as unchanged 5-ASA and 3-35% as N-acetyl-5-ASA. The mean elimination half-life was five hours (CV=73%) for 5-ASA and six hours (CV=63%) for N-acetyl-5-ASA following the initial dose. At steady state, the mean elimination half-life was seven hours for both 5-ASA and N-acetyl-5-ASA (CV=102% for 5-ASA and 82% for N-acetyl-5-ASA).

Drug-Drug Interactions:

The potential for interactions between mesalamine, administered as 1000 mg rectal suppositories, and other drugs has not been studied.

Special Populations (Patients with Renal or Hepatic Impairment):

The effect of renal or hepatic impairment on elimination of mesalamine in ulcerative proctitis patients treated with mesalamine 1000 mg suppositories has not been studied.

Preclinical Toxicology

Preclinical studies of mesalamine were conducted in rats, mice, rabbits and dogs, and kidney was the main target organ of toxicity. In rats, adverse renal effects were observed at a single oral dose of 600 mg/kg (about 3.2 times the recommended human intra-rectal dose, based on body surface area) and at IV doses of >214 mg/kg (about 1.2 times the recommended human intra-rectal dose, based on body surface area). In a 13-week oral gavage toxicity study in rats, papillary necrosis and/or multifocal tubular injury were observed in males receiving 160 mg/kg (about 0.86 times the recommended human intra-rectal dose, based on body surface area) and in both males and females at 640 mg/kg (about 3.5 times the recommended human intra-rectal dose, based on body surface area). In a combined 52-week toxicity and 127-week carcinogenicity study in rats, degeneration of the kidneys and hyalinization of basement membranes and Bowman’s capsule were observed at oral doses of 100 mg/kg/day (about 0.54 times the recommended human intra-rectal dose, based on body surface area) and above. In a 14-day rectal toxicity study of mesalamine suppositories in rabbits, intra-rectal doses up to 800 mg/kg (about 8.6 times the recommended human intra-rectal dose, based on body surface area) was not associated with any adverse effects. In a six-month oral toxicity study in dogs, doses of 80 mg/kg (about 1.4 times the recommended human intra-rectal dose, based on body surface area) and higher caused renal pathology similar to that described for the rat. In a rectal toxicity study of mesalamine suppositories in dogs, a dose of 166.6 mg/kg (about 3.0 times the recommended human intra-rectal dose, based on body surface area) produced chronic nephritis and pyelitis. In the 12-month eye toxicity study in dogs, Keratoconjunctivitis sicca (KCS) occurred at oral doses of 40 mg/kg (about 0.72 times the recommended human intra-rectal dose, based on body surface area) and above.

CLINICAL STUDIES

Two double-blind placebo-controlled multicenter studies were conducted in North America in patients with mild to moderate active ulcerative proctitis. The primary measures of efficacy were the same in all trials (clinical disease activity index, sigmoidoscopic and histologic evaluations). The main difference between the studies was dosage regimen: 500 mg three times daily (1.5 g/d) in Study 1; and 500 mg twice daily (1.0 g/d) in Study 2. A total of 173 patients were studied (Study 1, N=79; Study 2, N=94). Eighty-nine (89) patients received mesalamine suppositories, and eighty-four (84) patients received placebo suppositories. Patients were evaluated clinically and sigmoidoscopically after three and six weeks of suppository treatment. In Study No. 1 patients were 17 to 73 years of age (mean = 39 yrs), 57% were female, and 97% were white. Patients had an average extent of proctitis (upper disease boundary) of 10.8 cm. Eighty-four percent (84%) of the study patients had multiple prior episodes of proctitis. In Study No. 2, patients were 21 to 72 years of age (mean = 39 yrs), 62% were female, and 96% were white. Patients had an average extent of proctitis (upper disease boundary) of 10.3 cm. Seventy-eight percent (78%) of the study patients had multiple prior episodes of proctitis.

Compared to placebo, mesalamine suppository treatment was statistically (p less than 0.01) superior to placebo in all trials with respect to improvement in stool frequency, rectal bleeding, mucosal appearance, disease severity, and overall disease activity after three and six weeks of treatment. Daily diary records indicated significant improvement in rectal bleeding in the first week of therapy while tenesmus and diarrhea improved significantly within two weeks. Investigators rated patients receiving mesalamine much improved compared to patients receiving placebo (p less than 0.001).

The effectiveness of mesalamine suppositories was statistically significant irrespective of sex, extent of proctitis, duration of current episode or duration of disease.

A multicenter, open-label, randomized, parallel group study in ninety-nine (99) patients diagnosed with mild to moderate ulcerative proctitis compared the clinical efficacy of the CANASA® 1000 mg suppository to that of the CANASA ® 500 mg suppository. The primary measures of efficacy included clinical disease activity index, sigmoidoscopic and histologic evaluations. Patients were randomized to one of two treatment groups, with a dosage regimen of one 500 mg mesalamine suppository BID, morning and HS, or one 1000 mg mesalamine suppository HS for 6 weeks. Patients were evaluated clinically and sigmoidoscopically after three and six weeks of suppository treatment. Of the eighty-one (81) patients in the Per Protocol population, forty-six (46) patients received mesalamine 500 mg suppositories BID, and thirty-five (35) patients received mesalamine 1000 mg suppositories HS.

The efficacy of the 1000 mg HS treatment was not statistically or clinically different after 6 weeks from the 500 mg BID treatment, and both were effective in the treatment of ulcerative proctitis. Both treatments resulted in a significant decrease between Baseline and 6 weeks in the Disease Activity Index (DAI), a composite index reflecting rectal bleeding, stool frequency, mucosal appearance at endoscopy, and a global assessment of disease. In the 500 mg BID group, the mean DAI value decreased from 6.6 to 1.6, and in the 1000 mg HS group, the mean DAI value decreased from 6.2 to 1.3 over 6 weeks of treatment, representing a decrease of greater than 75% in both groups. Seventy-eight percent (78%; 36/46) of patients in the 500 mg BID group and 86% (30/35) of the patients in the 1000 mg HS group achieved a substantial improvement in symptoms (defined as a DAI score of less than 3) after 6 weeks of treatment. These patients regained normal daily stools, lost their rectal bleeding, and lost signs of inflammation at endoscopic visualization. The time to onset of response to the study drug was within 3 weeks of initiation of therapy in each treatment group, but further improvement was observed between 3 and 6 weeks of treatment.

INDICATIONS AND USAGE

CANASA® 1000 mg Suppositories are indicated for the treatment of active ulcerative proctitis.

CONTRAINDICATIONS

CANASA® 1000 mg Suppositories are contraindicated in patients who have demonstrated hypersensitivity to mesalamine (5-aminosalicylic acid) or to the suppository vehicle [saturated vegetable fatty acid esters (Hard Fat, NF)], or to salicylates (including aspirin).

PRECAUTIONS

Mesalamine has been implicated in the production of an acute intolerance syndrome characterized by cramping, acute abdominal pain and bloody diarrhea, sometimes fever, headache and a rash; in such cases prompt withdrawal is required. The patient’s history of sulfasalazine intolerance, if any, should be re-evaluated. If a rechallenge is performed later in order to validate the hypersensitivity, it should be carried out under close supervision and only if clearly needed, giving consideration to reduced dosage. In the literature, one patient previously sensitive to sulfasalazine was rechallenged with 400 mg oral mesalamine; within eight hours she experienced headache, fever, intensive abdominal colic, profuse diarrhea and was readmitted as an emergency. She responded poorly to steroid therapy and two weeks later a pancolectomy was required. The possibility of increased absorption of mesalamine and concomitant renal tubular damage as noted in the preclinical studies must be kept in mind. Patients on CANASA® 1000 mg, especially those on concurrent oral products which contain or release mesalamine and those with pre-existing renal disease, should be carefully monitored with urinalysis, BUN and creatinine testing.

In a clinical trial most patients who were hypersensitive to sulfasalazine were able to take mesalamine enemas without evidence of any allergic reaction. Nevertheless, caution should be exercised when mesalamine is initially used in patients known to be allergic to sulfasalazine. These patients should be instructed to discontinue therapy if signs of rash or fever become apparent.

A small proportion of patients have developed pancolitis while using mesalamine. However, extension of upper disease boundary and/or flare-ups occurred less often in the mesalamine-treated group than in the placebo-treated group.

Rare instances of pericarditis have been reported with mesalamine containing products including sulfasalazine. Cases of pericarditis have also been reported as manifestations of inflammatory bowel disease. In the cases reported there have been positive rechallenges with mesalamine or mesalamine containing products. In one of these cases, however, a second rechallenge with sulfasalazine was negative throughout a 2 month follow-up. Chest pain or dyspnea in patients treated with mesalamine should be investigated with this information in mind. Discontinuation of CANASA® suppositories may be warranted in some cases, but rechallenge with mesalamine can be performed under careful clinical observation should the continued therapeutic need for mesalamine be present.

There have been two reports in the literature of additional serious adverse events: one patient who developed leukopenia and thrombocytopenia after seven months of treatment with one 500 mg suppository nightly, and one patient with rash and fever which was a similar reaction to sulfasalazine.

Information for Patients:

See patient information printed at the end of this insert.

Carcinogenesis, Mutagenesis, Impairment of Fertility

Mesalamine caused no increase in the incidence of neoplastic lesions over controls in a two-year study of Wistar rats fed up to 320 mg/kg/day of mesalamine admixed with diet (about 1.7 times the recommended human intra-rectal dose, based on body surface area).

Mesalamine was not mutagenic in the Ames test, the mouse lymphoma cell (TK±) forward mutation test, or the mouse micronucleus test.

No effects on fertility or reproductive performance of the male and female rats were observed at oral mesalamine doses up to 320 mg/kg/day (about 1.7 times the recommended human intra-rectal dose, based on body surface area). The oligospermia and infertility in men associated with sulfasalazine have not been reported with mesalamine.

Pregnancy Teratogenic Effects, Pregnancy Category B

Teratology studies have been performed in rats at oral doses up to 320 mg/kg/day (about 1.7 times the recommended human intra-rectal dose, based on body surface area) and in rabbits at oral doses up to 495 mg/kg/day (about 5.4 times the recommended human intra-rectal dose, based on body surface area) and have revealed no evidence of impaired fertility or harm to the fetus due to mesalamine. There are, however, no adequate and well controlled studies in pregnant women. Because animal reproduction studies are not always predictive of human response, this drug should be used in pregnancy only if clearly needed.

Nursing Mothers

It is not known whether mesalamine or its metabolite(s) are excreted in human milk. Because many drugs are excreted in human milk, caution should be exercised when CANASA® 1000 mg suppositories are administered to a nursing woman.

Pediatric Use

Safety and effectiveness in pediatric patients have not been established.

Geriatric Use

Clinical studies of CANASA® did not include sufficient numbers of subjects aged 65 and over to determine whether they respond differently from younger subjects. Other reported clinical experience has not identified differences in responses between the elderly and younger patients. In general, dose selection for an elderly patient should be cautious, reflecting the greater frequency of decreased hepatic, renal, or cardiac function, and of concomitant disease or other drug therapy.

Mesalamine is known to be substantially excreted by the kidney, and the risk of toxic reactions to this drug may be greater in patients with impaired renal function. Because elderly patients are more likely to have decreased renal function, it may be useful to monitor renal function.

ADVERSE REACTIONS

Clinical Adverse Experience

The most frequent adverse reactions observed in the double-blind, placebo-controlled trials are summarized in the Table below.

ADVERSE REACTIONS OCCURRING IN MORE THAN 1% OF MESALAMINE SUPPOSITORY TREATED PATIENTS (COMPARISON TO PLACEBO)
Symptom | Mesalamine (n=177) | Placebo (n=84)
N | % | N | %
Dizziness | 5 | 3.0 | 2 | 2.4
Rectal Pain | 3 | 1.8 | 0 | 0.0
Fever | 2 | 1.2 | 0 | 0.0
Rash | 2 | 1.2 | 0 | 0.0
Acne | 2 | 1.2 | 0 | 0.0
Colitis | 2 | 1.2 | 0 | 0.0

In the multicenter, open-label, randomized, parallel group study comparing the CANASA® 1000 mg suppository (HS) to that of the CANASA® 500 mg suppository (BID), there were no differences between the two treatment groups in the adverse event profile. The most frequent AEs were headache (14.4%), flatulence (5.2%), abdominal pain (5.2%), diarrhea (3.1%), and nausea (3.1%). Three (3) patients had to discontinue medication because of a treatment emergent AE; one of these AEs (headache) was deemed possibly related to study medication.

In addition to the events observed in the clinical trials, the following adverse events have been associated with mesalamine containing products: nephrotoxicity, pancreatitis, fibrosing alveolitis and elevated liver enzymes. Cases of pancreatitis and fibrosing alveolitis have been reported as manifestations of inflammatory bowel disease as well.

Hair Loss

Mild hair loss characterized by “more hair in the comb” but no withdrawal from clinical trials has been observed in seven of 815 mesalamine patients but none of the placebo-treated patients. In the literature there are at least six additional patients with mild hair loss who received either mesalamine or sulfasalazine. Retreatment is not always associated with repeated hair loss.

OVERDOSAGE

There have been no documented reports of serious toxicity in man resulting from massive overdosing with mesalamine. Under ordinary circumstances, mesalamine absorption from the colon is limited.

DOSAGE AND ADMINISTRATION

The usual dosage of CANASA® (mesalamine, USP) 1000 mg suppositories is one rectal suppository 1 time daily at bedtime.

The suppository should be retained for one to three hours or longer, if possible, to achieve the maximum benefit. While the effect of CANASA® suppositories may be seen within three to twenty-one days, the usual course of therapy would be from three to six weeks depending on symptoms and sigmoidoscopic findings. Studies have suggested that CANASA® suppositories will delay relapse after the six-week short-term treatment.

Patient Instructions:

NOTE: CANASA® suppositories will cause staining of direct contact surfaces, including but not limited to fabrics, flooring, painted surfaces, marble, granite, vinyl, and enamel.

1. Detach one suppository from strip of suppositories.
2. Hold suppository upright and carefully remove the plastic wrapper.
3. Avoid excessive handling of suppository, which is designed to melt at body temperature.
4. Insert suppository completely into rectum with gentle pressure, pointed end first.
5. A small amount of lubricating gel may be used on the tip of the suppository to assist insertion.

HOW SUPPLIED

CANASA® (Mesalamine, USP) 1000 mg Suppositories: CANASA® 1000 mg Suppositories for rectal administration are available as bullet shaped, light tan suppositories containing 1000 mg mesalamine supplied in boxes of 30 plastic wrapped suppositories (NDC 54868-6147-0).

Store below 25°C (77°F), do not freeze. Keep away from direct heat, light or humidity.

Rx only

Axcan Pharma US, Inc.

Birmingham, AL 35242

Date: May 2008

Relabeling of "Additional Barcode Label" by:
Physicians Total Care, Inc.
Tulsa, OK 74146

Patient Information

CANASA® Rectal Suppositories

(Mesalamine, USP) 1000 mg

Read this information carefully before you begin treatment. Also, read the information you get whenever you get more medicine. There may be new information. This information does not take the place of talking with your doctor about your medical condition or your treatment. If you have any questions about this medicine, ask your doctor or pharmacist.

What is CANASA®?

CANASA® (can-AH-sah) is a medicine used to treat ulcerative proctitis (ulcerative rectal colitis). CANASA® works inside your rectum (lower intestine) to help reduce bleeding, mucous and bloody diarrhea caused by inflammation (swelling and soreness) of the rectal area. You use CANASA® by inserting it into your rectum.

Who should not use CANASA®?

Do not use CANASA® if you are allergic to the active ingredient mesalamine (also found in drugs such as Rowasa, Asacol, Pentasa, Azulfidine, and Dipentum), if you are allergic to the inactive ingredients, or if you have had any unusual reaction to the ingredients.

Tell your doctor if you:

- Have kidney problems. Using CANASA® may make them worse.
- Have had inflamed pancreas (pancreatitis).
- Are pregnant. You and your doctor will decide if you should use CANASA®.
- Have ever had pericarditis (inflamed sac around your heart).
- Are allergic to sulfasalazine. You may need to watch for signs of an allergic reaction to CANASA®.
- Are allergic to aspirin.
- Are allergic to other things, such as foods, preservatives, or dyes.

How should I use CANASA®?

Follow your doctor’s instructions about how often to use CANASA® and how long to use it. For the 1000 mg suppository, the usual dose is one suppository at bedtime for 3-6 weeks. We do not know if CANASA® will work for children or is safe for them.

Follow these steps to use CANASA®:

1. For best results, empty your rectum (have a bowel movement) just before using CANASA®.
2. Detach one CANASA® suppository from the strip of suppositories.
3. Hold the suppository upright and carefully peel open the plastic at the pre-cut line to take out the suppository.
4. Insert the suppository with the pointed end first completely into your rectum, using gentle pressure.
5. For best results, keep the suppository in your rectum for 3 hours or longer, if possible.

If you have trouble inserting CANASA®, you may put a little bit of lubricating gel on the suppository.

Do not handle the suppository too much, since it may begin to melt from the heat from your hands and body.

If you miss a dose of CANASA®, use it as soon as possible, unless it is almost time for next dose. Do not use two CANASA® suppositories at the same time to make up for a missed dose.

Keep using CANASA® as long as your doctor tells you to use it, even if you feel better.

CANASA® can cause stains on things it touches. Therefore keep it away from clothing and other fabrics, flooring, painted surfaces, marble, granite, plastics, andenamel. Be careful since CANASA® may stain clothing.

What should I avoid while taking CANASA®?

Do not breast feed while using CANASA®. We do not know if CANASA® can pass through the milk and harm the baby. Tell your doctor if you become pregnant while using CANASA®.

What are the possible side effects of CANASA®?

- The most common side effects of CANASA® are: headache, gas or flatulence, and diarrhea. These events also occurred when patients were given an inactive suppository.
- Less common, but possibly serious side effects include a reaction to the medicine (acute intolerance syndrome) that includes cramps, sharp abdominal (stomach area) pain, bloody diarrhea, and sometimes fever, headache and rash. Stop use and tell your doctor right away if you get any of these symptoms.
- In rare cases, the sac around the heart may become inflamed (pericarditis). Tell your doctor right away if you develop chest pain or shortness of breath, which are signs of this problem.
- In rare cases, patients using CANASA® develop worsening colitis (pancolitis).
- A very few patients using CANASA® may have mild hair loss.
- Other side effects not listed above may also occur in some patients.

If you notice any other side effects, check with your doctor or pharmacist.

How should I store CANASA®?

Store CANASA® below 25°C (77°F), do not freeze it. Keep it away from direct heat, light, or humidity. Keep it out of the reach of children.

General advice about prescription medicines

Medicines are sometimes prescribed for conditions that are not mentioned in patient information leaflets. Do not use CANASA® for a condition for which it was not prescribed. Do not give CANASA® to other people, even if they have the same symptoms you have.

This leaflet summarizes the most important information about CANASA®. If you would like more information, talk with your doctor. You can ask your pharmacist or doctor for information about CANASA® that is written for health professionals.

PRINCIPAL DISPLAY PANEL

CANASA® (Mesalamine, USP) 1000 mg Suppositories